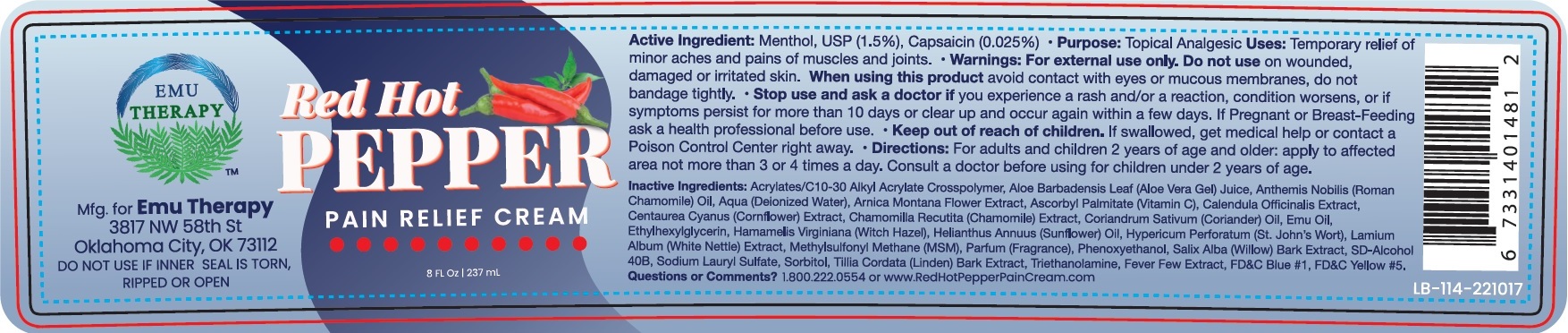 DRUG LABEL: EMU THERAPY Red Hot Pepper Pain Relief Cream
NDC: 83591-417 | Form: CREAM
Manufacturer: ACA MANAGEMENT LLC
Category: otc | Type: HUMAN OTC DRUG LABEL
Date: 20231106

ACTIVE INGREDIENTS: MENTHOL 15 mg/1 mL; CAPSAICIN 0.25 mg/1 mL
INACTIVE INGREDIENTS: ALOE VERA LEAF; WATER; ARNICA MONTANA FLOWER; ASCORBYL PALMITATE; CALENDULA OFFICINALIS FLOWER; CHAMOMILE; CORIANDER; EMU OIL; ETHYLHEXYLGLYCERIN; HAMAMELIS VIRGINIANA ROOT BARK/STEM BARK; HELIANTHUS ANNUUS FLOWERING TOP; HYPERICUM PERFORATUM WHOLE; LAMIUM ALBUM WHOLE; DIMETHYL SULFONE; PHENOXYETHANOL; SALIX ALBA BARK; SODIUM LAURYL SULFATE; SORBITOL; TROLAMINE; TANACETUM PARTHENIUM WHOLE; FD&C BLUE NO. 1; FD&C YELLOW NO. 5

EMU THERAPY Red Hot Pepper Pain Relief Cream

Active Ingredient:

Menthol, USP (2.75%)

Capsaicin (0.025%)

Purpose:

Topical Analgesic

Uses:

Temporary relief of minor aches and pains of muscles and joints.

Warnings:

- For external use only.

Do not use

on wounded, damaged or irritated skin.

When using this product

avoid contact with eyes or mucous membranes, do not bandage tightly.

Stop use and ask a doctor

- if you experience a rash and/or a reaction, condition worsens, or if symptoms persist for more than 10 days or clear up and occur again within a few days.

If pregnant or Breast-Feeding

- ask a health professional before use.

Keep out of reach of children.

If swallowed, get medical help or contact a Poison Control Center right away.

Directions:

- For adults and children 2 years of age and older: apply to affected area not more than 3 or 4 times a day. Consult a doctor before using for children under 2 years of age.

Inactive Ingredients:

Acrylates/C10-30 Alkyl Acrylate Crosspolymer, Aloe Barbadensis Leaf (Aloe Vera Gel) Juice, Anthemis Nobilis (Roman Chamomile) Oil, Aqua (Deionized Water), Arnica Montana Flower Extract, Ascorbyl Palmitate (Vitamin C), Calendula Officinalis Extract, Centaurea Cyanus (Corniflower) Extract, Chamomilla Recutita (Chamomile) Extract, Coriandrum Sativum (Coriander) Oil, Emu Oil, Ethylhexylglycerin, Hamamelis Virginiana (Witch Hazel), Helianthus Annuus (Sunflower) Oil, Hypericum Perforatum (St. John's Wort), Lamium Album (White Nettle) Extract, Methylsulfonyl Methane (MSM), Parfum (Fragrance), Phenoxyethanol, Salix Alba (Willow) Bark Extract, SD-Alcohol 40B, Sodium Lauryl Sulfate, Sorbitol, Tillia Cordata (Linden) Bark Extract, Triethanolamine, Fever Few Extract, FD&C Blue #1, FD&C Yellow #5.

Questions or Comments?

1-800-222-0554 or www.RedHotPepperPainCream.com